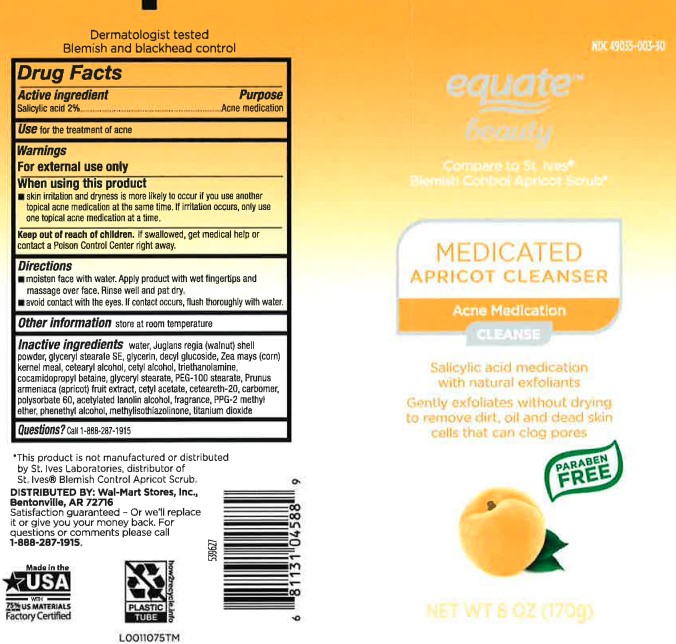 DRUG LABEL: Medicated Apricot Scrub
NDC: 49035-003 | Form: GEL
Manufacturer: Walmart Inc.
Category: otc | Type: HUMAN OTC DRUG LABEL
Date: 20260227

ACTIVE INGREDIENTS: SALICYLIC ACID 20 mg/1 g
INACTIVE INGREDIENTS: WATER; JUGLANS REGIA SHELL; GLYCERYL STEARATE SE; GLYCERIN; DECYL GLUCOSIDE; CORN GRAIN; CETOSTEARYL ALCOHOL; CETYL ALCOHOL; TROLAMINE; COCAMIDOPROPYL BETAINE; GLYCERYL MONOSTEARATE; PEG-100 STEARATE; APRICOT; CETYL ACETATE; CARBOMER HOMOPOLYMER TYPE C (ALLYL PENTAERYTHRITOL CROSSLINKED); POLYSORBATE 60; POLYOXYL 20 CETOSTEARYL ETHER; ACETYLATED LANOLIN ALCOHOLS; PPG-2 METHYL ETHER; .ALPHA.-ISOBUTYLPHENETHYL ALCOHOL; METHYLISOTHIAZOLINONE; TITANIUM DIOXIDE

Equate 041.005/041AF-AJ
Medicated Apricot Scrub

Claims

Dermatologist tested

Blemish and blackhead control

Active ingredient

Salicylic acid 2%

Purpose

Acne medication

Use

for the treatment of acne

Warnings

For external use only

When using this product

skin irritation and dryness is more likely to occur if you use another topical acne medication at the same time. If irritation occurs, only use one topical acne medication at a time.

Keep out of reach of children.

If swallowed, get medical help or contact a Poison Control Center right away.

Directions

- moisten face with water. Apply product with wet fingertips and massage over face. Rinse well and pat dry.
- avoid contact with the eyes. If contact occurs, flush thoroughly with water.

Other information

Store at room temperature

Inactive ingredients

water, Juglans regia (walnut) shell powder, glyceryl stearate SE, glycerin, decyl glucoside, Zea mays (corn) kernel meal, cetearyl alcohol, cetyl alcohol, triethanolamine, cocamidopropyl betaine, glyceryl stearate, PEG-100 stearate, Prunus armeniaca (apricot) fruit extract, cetyl acetate, ceteareth-20, carbomer, polysorbate 60, acetylated lanolin alcohol, fragrance, PPG-2 methyl ether, phenethyl alcohol, methylisothiazolinone, titanium dioxide

Questions?

Call 1-888-287-1915

Disclaimer

*This product is not manufactured or distributed by St. Ives Laboratories, distributor of St. Ives®Blemish Control Apricot Scrub.

Distributed by: Wal-Mart Stores, Inc.,

Bentonville, AR 72716

Satisfaction guaranteed - Or we'll replace it or give you your money back. For questions or comments please call 1-888-287-1915.

Made in the USA with 75% US Materials

Factory Certified

PLASTIC TUBE

how2recycle.info

principal display panel

NDC 49035-003-30

equate™ beauty

COMPARE TO ST. IVES®BLEMISH CONTROL APRICOT SCRUB*

Medicated

Apricot Cleanser

Acne Medication

CLEANSE

Salicylic acid acne medication with natural exfoliants

Gently exfoliates without drying to remove dirt, oil and dead skin cells that can clog pores

Paraben Free

NET WT 6 OZ (170 g)